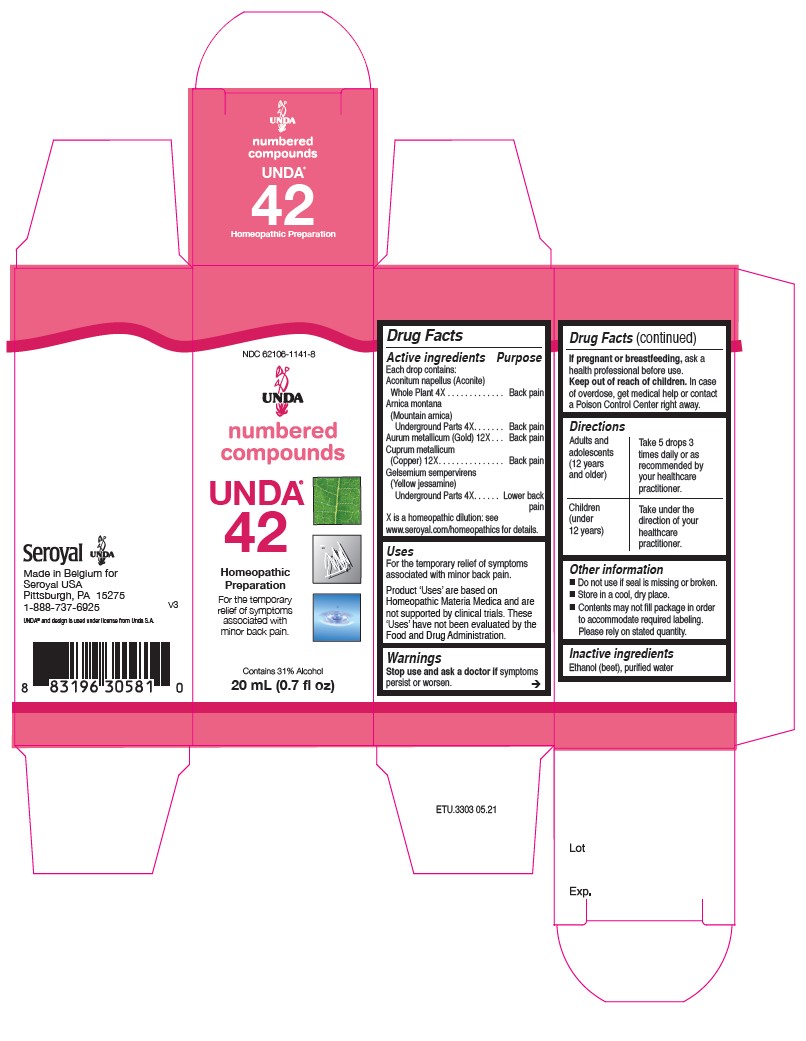 DRUG LABEL: Unda 42
NDC: 62106-1141 | Form: LIQUID
Manufacturer: Seroyal USA
Category: homeopathic | Type: HUMAN OTC DRUG LABEL
Date: 20210715

ACTIVE INGREDIENTS: GELSEMIUM SEMPERVIRENS ROOT 4 [hp_X]/20 mL; ACONITUM NAPELLUS 4 [hp_X]/20 mL; GOLD 12 [hp_X]/20 mL; ARNICA MONTANA 4 [hp_X]/20 mL; COPPER 12 [hp_X]/20 mL
INACTIVE INGREDIENTS: WATER; ALCOHOL

Unda 42

Active ingredients
Each drop contains equal parts of:
Aconitum napellus (Aconite) Whole Plant 4X
Arnica montana (Mountain arnica) Root 4X
Aurum metallicum (Gold) 12X
Cuprum metallicum (Copper) 12X
Gelsemium sempervirens (Yellow jessamine) Root 4X

Uses
For the relief of symptoms
associated with minor back pain.

Warnings

Stop use and ask a doctor if symptoms persist or worsen.

If pregnant or breastfeeding, ask a health professional before use.

Keep out of reach of children.

In case of overdose, get medical help or contact a
Poison Control Center right away.

PREGNANCY OR BREAST FEEDING

If pregnant or breastfeeding, ask a health professional before use.

Keep out of reach of children.

OVERDOSAGE

In case of overdose, get medical help or contact a
Poison Control Center right away.

Directions
Adults and adolescents (12 years and older)

Take 5 drops three times daily or as recommended by your healthcare practitioner.
Children (under 12 years)

Take under the direction of your healthcare practitioner.

Indications
For the relief of symptoms associated with minor back pain.

Directions
Adults and adolescents (12 years and older)

Take 5 drops three times daily or as recommended by your healthcare practitioner.
Children (under 12 years)

Take under the direction of your healthcare practitioner.

Other information
Do not use if seal is missing or broken.
Store in a cool, dry place.

Contents may not fill package in order
to accommodate required labeling.
Please rely on stated quantity.

Inactive Ingredients:

Ethanol (beet),
purified water

PACKAGE LABEL

NDC 62106-1141-8

UNDA

numbered compounds

UNDA 42

Homeopathic Preparation

For the temporary relief of symptoms
associated with minor back pain.

Contains 31% Alcohol

0.7 fl oz (20 mL)